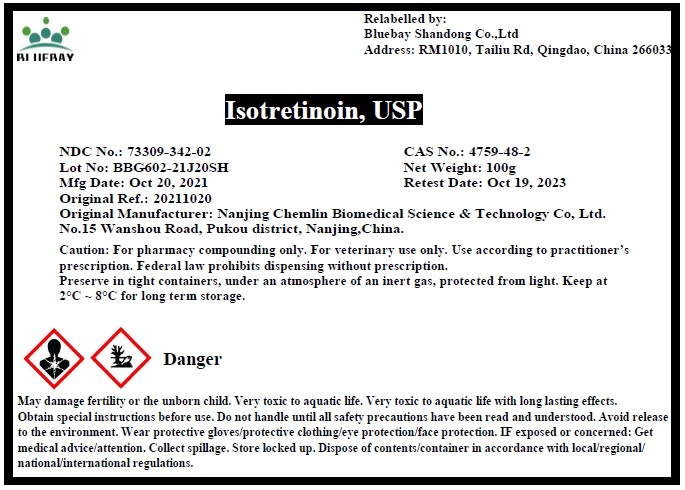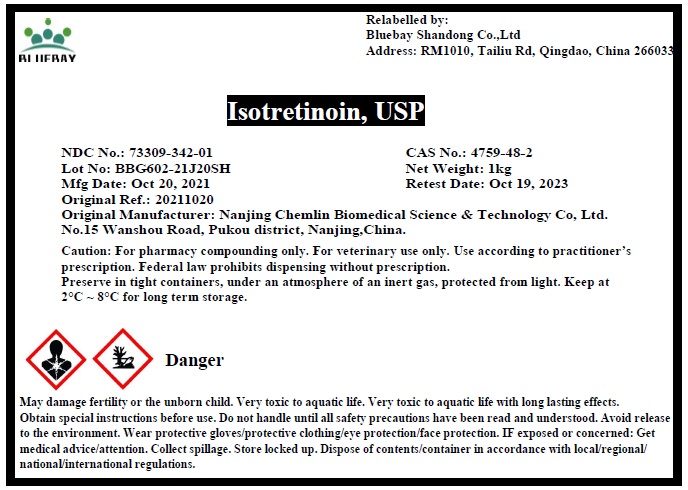 DRUG LABEL: Isotretinoin
NDC: 73309-342 | Form: POWDER
Manufacturer: BLUEBAY SHANDONG CO.,LTD
Category: other | Type: BULK INGREDIENT
Date: 20211119

ACTIVE INGREDIENTS: ISOTRETINOIN 1 g/1 g

Isotretinoin